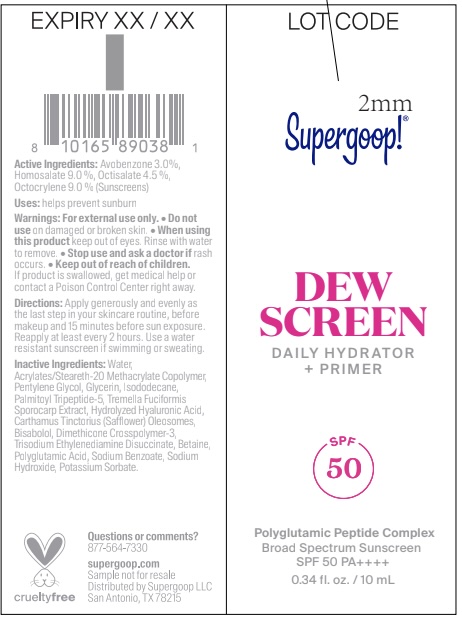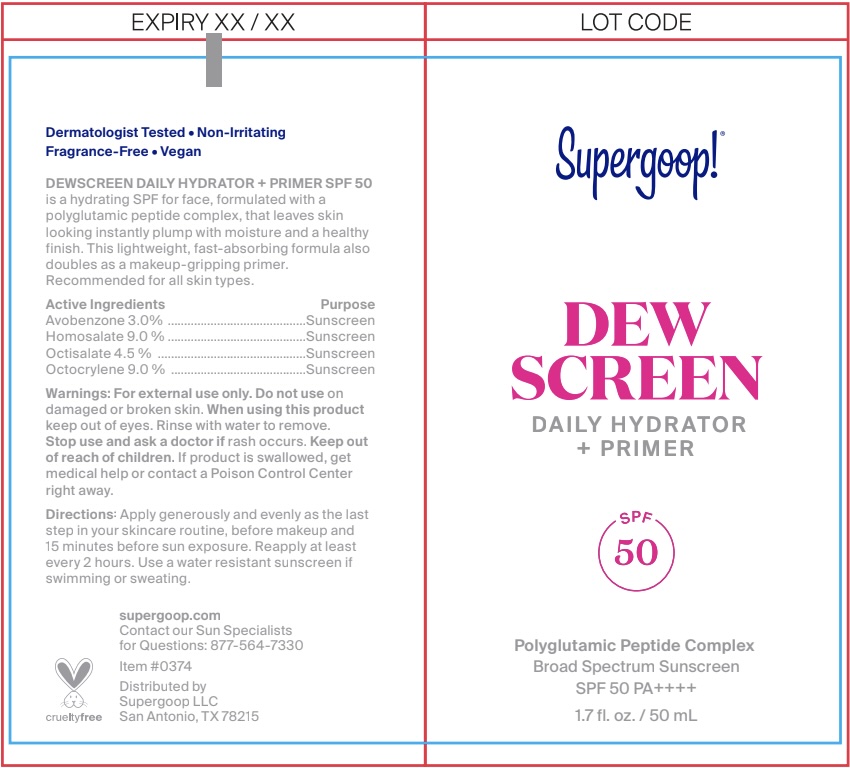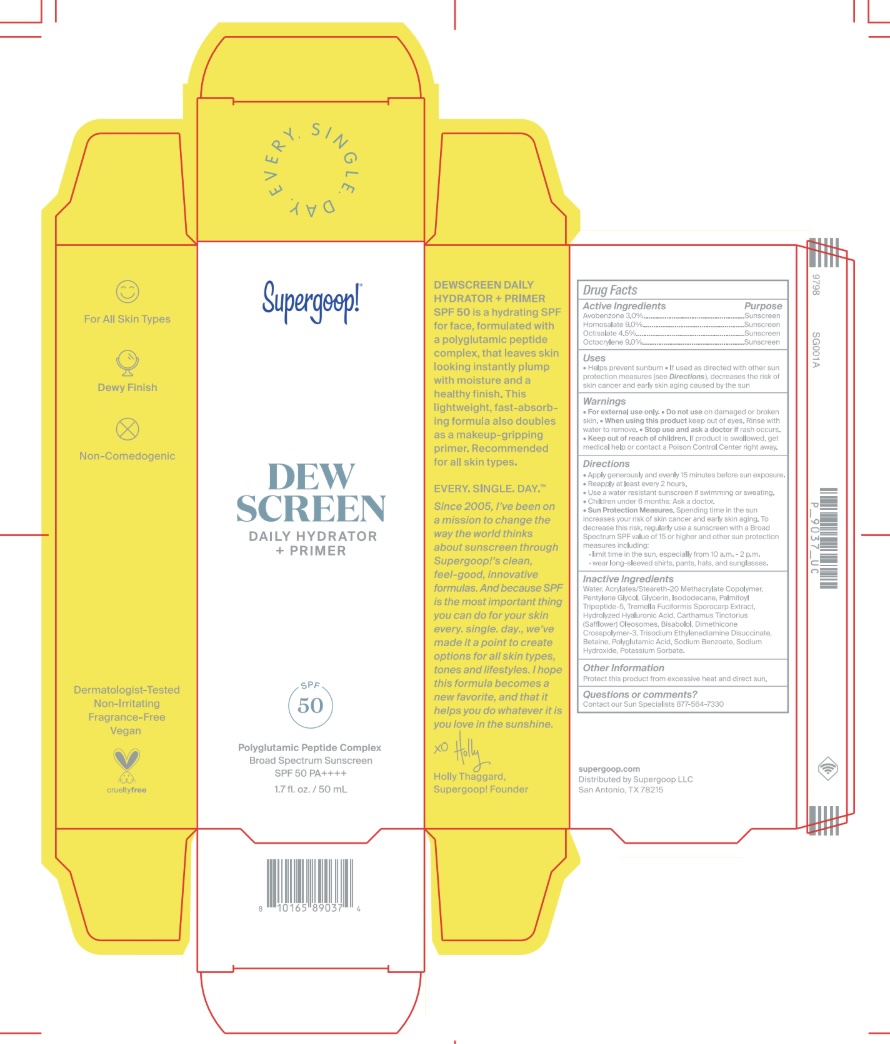 DRUG LABEL: Dewscreen Daily Hydrator and Primer SPF 50
NDC: 75936-660 | Form: LOTION
Manufacturer: Supergoop LLC
Category: otc | Type: HUMAN OTC DRUG LABEL
Date: 20250923

ACTIVE INGREDIENTS: AVOBENZONE 3 mg/100 mL; HOMOSALATE 9 mg/100 mL; OCTISALATE 4.5 mg/100 mL; OCTOCRYLENE 9 mg/100 mL
INACTIVE INGREDIENTS: CARTHAMUS TINCTORIUS SEED OLEOSOMES; BISABOLOL; PHENOXYETHANOL; POLYGLUTAMIC ACID (1200 MW); WATER; SODIUM BENZOATE; SODIUM HYDROXIDE; DIMETHICONE CROSSPOLYMER; PALMITOYL TRIPEPTIDE-5; ACRYLATES/STEARETH-20 METHACRYLATE COPOLYMER; TRISODIUM ETHYLENEDIAMINE DISUCCINATE; TREMELLA FUCIFORMIS FRUITING BODY; POTASSIUM SORBATE; HYALURONIC ACID; BETAINE; PENTYLENE GLYCOL; GLYCERIN; ISODODECANE

Dewscreen Daily Hydrator + Primer SPF 50

Active Ingredients:

Avobenzone 3.0%
Homosalate 9.0%
Octisalate 4.5%
Octocrylene 9.0%

PURPOSE

Helps prevent sunburn

If used as directed with other sun protection measures (see Directions), decreases the risk of skin cancer and early skin aging caused by the sun

WARNINGS

For External use only

Do not use on damaged or broken skin

When using this product, keep out of eyes. Rinse with water to remove

Keep out of reach of children. If product is swallowed, get medical help, or contact a poison control center right away.

Directions

• Apply generously and evenly as the last step in your skincare routine, before makeup and 15 minutes before sun exposure. • Reapply at least every 2 hours. • Use a water resistant sunscreen if swimming or sweating. • Children under 6 months of age: ask a doctor. • Sun Protection Measures. Spending time in the sun increases your risk of skin cancer and early skin aging. To decrease this risk, regularly use a sunscreen with a Broad Spectrum SPF value of 15 or higher and other sun protection measures including: • limit time in the sun, especially from 10 a.m.-2 p.m. • wear long-sleeved shirts, pants, hats, and sunglasses.

Inactive Ingredients:

Water, Acrylates/Steareth-20 Methacrylate Copolymer, Pentylene Glycol, Glycerin, Isododecane, Palmitoyl Tripeptide-5, Tremella Fuciformis Sporocarp Extract, Hydrolyzed Hyaluronic Acid, Carthamus Tinctorius (Safflower) Oleosomes, Bisabolol, Dimethicone Crosspolymer-3, Trisodium Ethylenediamine Disuccinate, Betaine, Polyglutamic Acid, Sodium Benzoate, Sodium Hydroxide, Potassium Sorbate

Stop use and ask a doctor if rash occurs

PACKAGE LABEL

Supergoop!

DEW

SCREEN

Daily Hydrator

+ Primer

SPF 50

Polyglutamic Peptide Complex

Broad Spectrum Sunscreen

SPF 50 PA++++

1.7 fl. oz. / 50 mL or 0.34 fl. oz / 10 mL